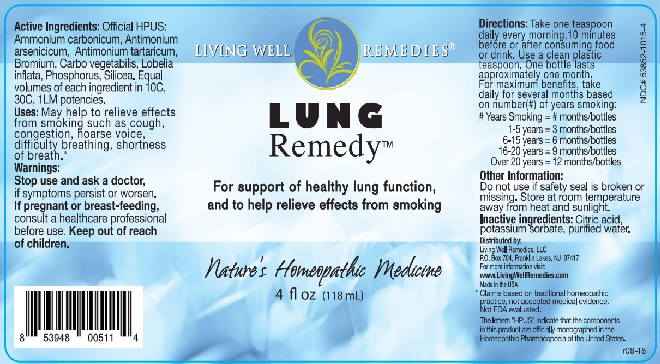 DRUG LABEL: Lung Remedy
NDC: 53852-1015 | Form: LIQUID
Manufacturer: Living Well Remedies, LLC
Category: homeopathic | Type: HUMAN OTC DRUG LABEL
Date: 20181008

ACTIVE INGREDIENTS: BROMINE 10 [hp_C]/118 mL; ACTIVATED CHARCOAL 10 [hp_C]/118 mL; LOBELIA INFLATA 10 [hp_C]/118 mL; PHOSPHORUS 10 [hp_C]/118 mL; SILICON DIOXIDE 10 [hp_C]/118 mL; AMMONIUM CARBONATE 10 [hp_C]/118 mL; ANTIMONY ARSENATE 10 [hp_C]/118 mL; ANTIMONY POTASSIUM TARTRATE 10 [hp_C]/118 mL
INACTIVE INGREDIENTS: CITRIC ACID MONOHYDRATE; POTASSIUM SORBATE; WATER

Lung Remedy

ACTIVE INGREDIENT

Active Ingredients: Official HPUS: Ammonium carbonicum, Antimonium arsenicicum, Antimonium tartaricum, Bromium, Carbo vegetabilis, Lobelia inflata, Phosphorus, Silicea. Equal volumes of each ingredient in 10C, 30C, 1LM potencies.

*Claims based on traditional homeopathic practice, not accepted medical evidence.

Not FDA evaluated.

The letters"HPUS" indicate that the componenets in this product are offically monographed in the Homeopathic Pharmacopoeia of the United States.

INDICATIONS AND USAGE

Uses: May help to relieve effects from smoking such as cough, congestion, hoarse voice, difficulty breathing, shortness of breath.*

WARNINGS

Warnings: Stop use and ask a doctor, if symptoms persist or worsen. If pregnant or breast-feeding, consult a health care professional before use.

Keep out of reach of children.

Directions:

Take one teaspoon daily every morning, 10 minutes before or after consuming food or drink. Use a clean plastic teaspoon. One bottle lasts approximately one month. For maximum benefits, take daily for several months based on number (#) of years smoking:

#Years Smoking = # months/bottles

1-5 years = 3 months/bottles

6-15 years = 6 months/bottles

16-20 years = 9 months/bottles

Over 20 years = 12 months/bottles

Other Information: Do not use if safety seal is broken or missing. Store at room temperature away from heat and sunlight.

Inactive ingredients: Citric acid, potassium sorbate, purified water.

QUESTIONS

Distributed by:

Living Well Remedies, LLC

P.O. Box 704, Franklin Lakes, NM 07417

For more information visit:

www.LivingWellRemedies.com

Made in the USA

PACKAGE LABEL

LIVING WELL REMEDIES®

LUNG

Remedy™

For support of healthy lung function,

and to help relieve effects from smoking

Nature's Homeopathic Medicine

4 fl oz (118mL)

PURPOSE

For suport of healthy lung function,

and to help relieve effects from smoking